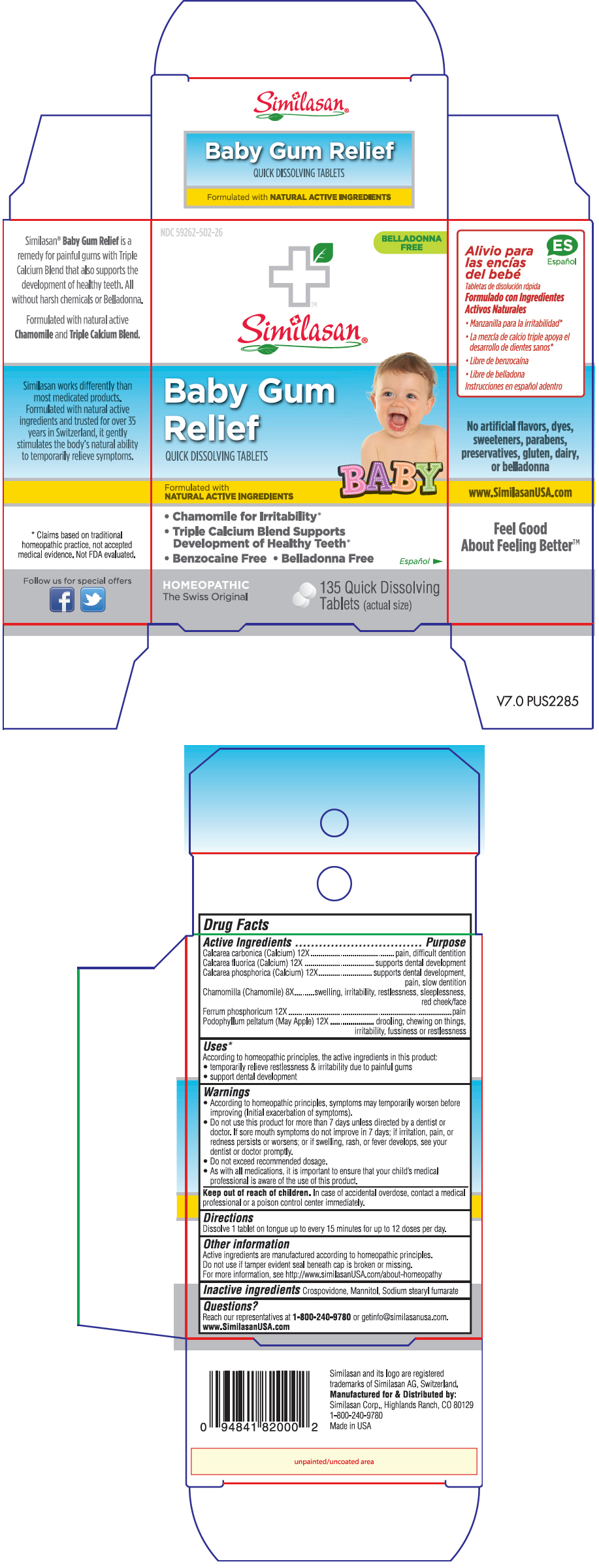 DRUG LABEL: BABY GUM RELIEF
NDC: 59262-502 | Form: TABLET, ORALLY DISINTEGRATING
Manufacturer: Similasan Corporation
Category: homeopathic | Type: HUMAN OTC DRUG LABEL
Date: 20180809

ACTIVE INGREDIENTS: OYSTER SHELL CALCIUM CARBONATE, CRUDE 12 [hp_X]/1 1; CALCIUM FLUORIDE 12 [hp_X]/1 1; TRIBASIC CALCIUM PHOSPHATE 12 [hp_X]/1 1; CHAMOMILE 8 [hp_X]/1 1; FERROSOFERRIC PHOSPHATE 12 [hp_X]/1 1; PODOPHYLLUM 12 [hp_X]/1 1
INACTIVE INGREDIENTS: CROSPOVIDONE, UNSPECIFIED; MANNITOL; SODIUM STEARYL FUMARATE

BABY GUM RELIEF

Drug Facts

ACTIVE INGREDIENT

Active Ingredients | Purpose
Calcarea carbonica (Calcium) 12X | pain, difficult dentition
Calcarea fluorica (Calcium) 12X | supports dental development
Calcarea phosphorica (Calcium) 12X | supports dental development, pain, slow dentition
Chamomilla (Chamomile) 8X | swelling, irritability, restlessness, sleeplessness, red cheek/face
Ferrum phosphoricum 12X | pain
Podophyllum peltatum (May Apple) 12X | drooling, chewing on things, irritability, fussiness or restlessness

Uses [Claims based on traditional homeopathic practice, not accepted medical evidence. Not FDA evaluated.]

According to homeopathic principles, the active ingredients in this product:

- temporarily relieve restlessness & irritability due to painful gums
- support dental development

Warnings

- According to homeopathic principles, symptoms may temporarily worsen before improving (Initial exacerbation of symptoms).
- Do not use this product for more than 7 days unless directed by a dentist or doctor. If sore mouth symptoms do not improve in 7 days; if irritation, pain, or redness persists or worsens; or if swelling, rash, or fever develops, see your dentist or doctor promptly.
- Do not exceed recommended dosage.
- As with all medications, it is important to ensure that your child's medical professional is aware of the use of this product.

Keep out of reach of children. In case of accidental overdose, contact a medical professional or a poison control center immediately.

Directions

Dissolve 1 tablet on tongue up to every 15 minutes for up to 12 doses per day.

Other information

Active ingredients are manufactured according to homeopathic principles.

Do not use if tamper evident seal beneath cap is broken or missing.

For more information, see http://www.similasanUSA.com/about-homeopathy

Inactive ingredients

Crospovidone, Mannitol, Sodium stearyl fumarate

Questions?

Reach our representatives at 1-800-240-9780 or getinfo@similasanusa.com. www.SimilasanUSA.com

Distributed by:
Similasan Corp., Highlands Ranch, CO 80129

PRINCIPAL DISPLAY PANEL - 135 Tablet Bottle Box

NDC 59262-502-26

BELLADONNA
FREE

Similasan®

Baby Gum
Relief

QUICK DISSOLVING TABLETS

Formulated with
NATURAL ACTIVE INGREDIENTS

BABY

- Chamomile for Irritability*
- Triple Calcium Blend Supports
  Development of Healthy Teeth*
- Benzocaine Free • Belladonna Free

HOMEOPATHIC
The Swiss Original

135 Quick Dissolving
Tablets (actual size)